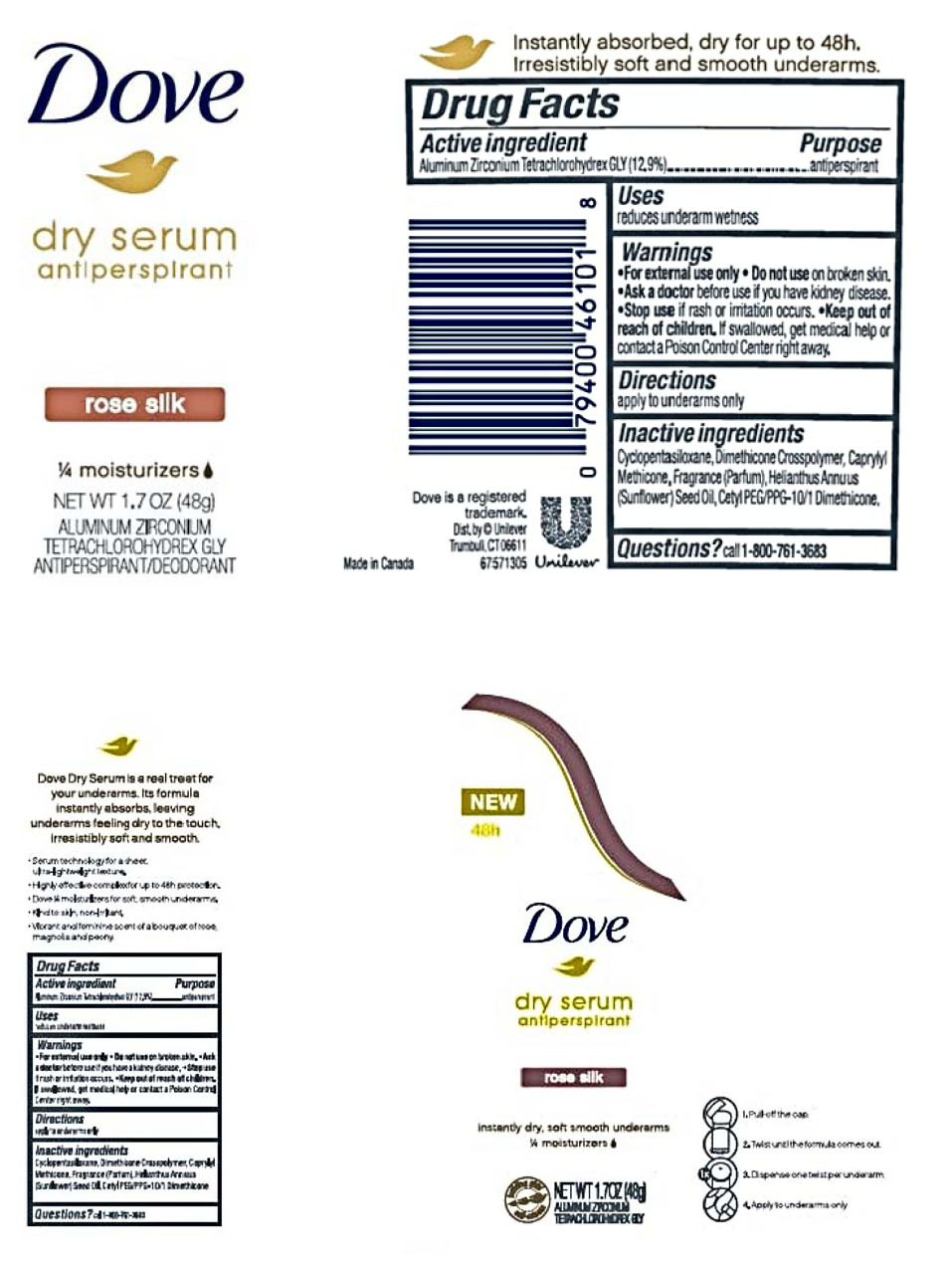 DRUG LABEL: Dove
NDC: 64942-1632 | Form: STICK
Manufacturer: CONOPCO Inc. d/b/a Unilever
Category: otc | Type: HUMAN OTC DRUG LABEL
Date: 20241024

ACTIVE INGREDIENTS: ALUMINUM ZIRCONIUM TETRACHLOROHYDREX GLY 12.9 g/100 g
INACTIVE INGREDIENTS: CAPRYLYL TRISILOXANE; CETYL PEG/PPG-10/1 DIMETHICONE (HLB 2); SUNFLOWER OIL; CYCLOMETHICONE 5

Dove Rose Silk Dry Serum Antiperspirant

DOVE ROSE SILK DRY SERUM ANTIPERSPIRANT - aluminum zirconium tetrachlorohydrex gly stick

Dove Rose Silk Dry Serum Antiperspirant

Drug Facts

Active Ingredients
Aluminum Zirconium Tetrachlorohydrex GLY (12.9 %)

Purpose

antiperspirant

Uses

• reduces underarm wetness

Warnings

• For external use only
• Do not use on broken skin
• Ask a doctor before use if you have kidney disease
• Stop use if rash or irritation occurs

• Keep out of reach of children.

If swallowed, get medical help or contact a Poison Control Center right away.

Directions

• apply to underarms only

Inactive ingredients

Cyclopentasiloxane, Dimethicone Crosspolymer, Caprylyl Methicone, Fragrance (Parfum), Helianthus Annuus (Sunflower) Seed Oil, Cetyl PEG/PPG-10/1 Dimethicone.

Questions?

Call toll-free 1-800-761-3683